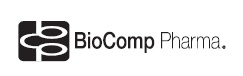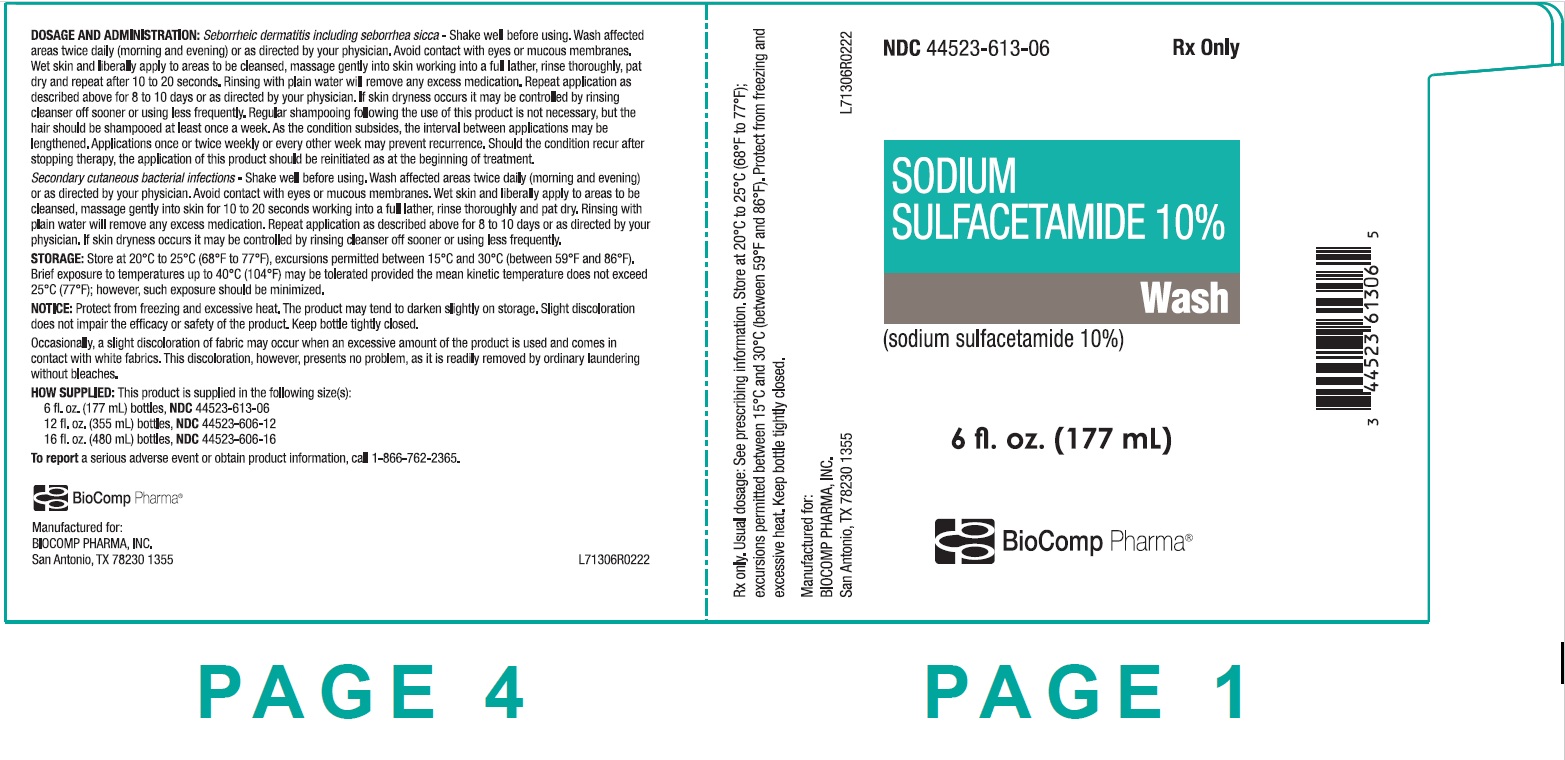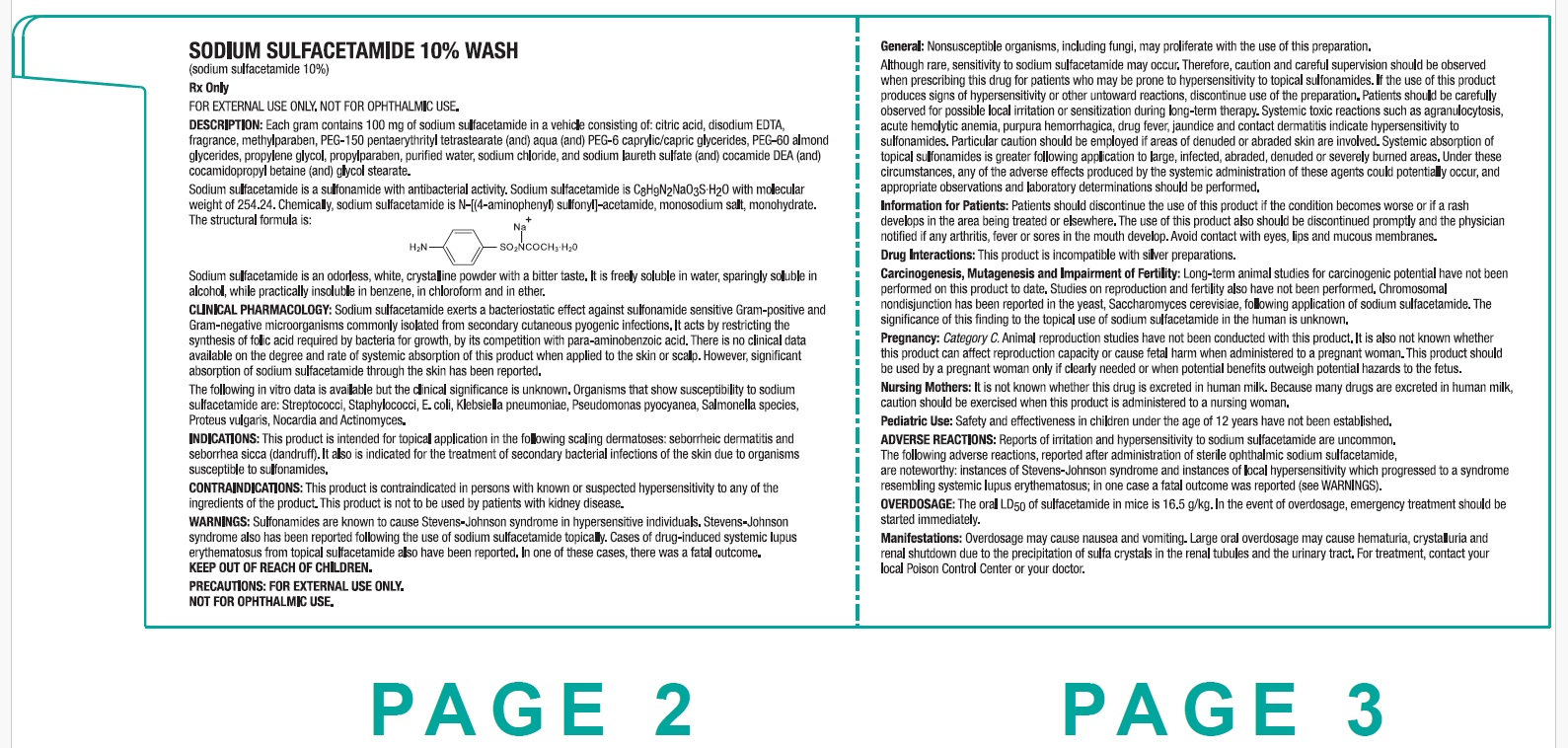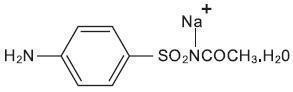 DRUG LABEL: SODIUM SULFACETAMIDE
NDC: 44523-613 | Form: LIQUID
Manufacturer: BioComp Pharma, Inc.
Category: prescription | Type: HUMAN PRESCRIPTION DRUG LABEL
Date: 20260112

ACTIVE INGREDIENTS: SULFACETAMIDE SODIUM 100 mg/1 mL

SODIUM SULFACETAMIDE 10% WASH

Rx Only
FOR EXTERNAL USE ONLY. NOT FOR OPHTHALMIC USE.

DESCRIPTION:

Each gram contains 100 mg of sodium sulfacetamide in a vehicle consisting of: citric acid, disodium EDTA, fragrance, methylparaben, PEG-150 pentaerythrityl tetrastearate (and) aqua (and) PEG-6 caprylic/capric glycerides, PEG-60 almond glycerides, propylene glycol, propylparaben, purified water, sodium chloride, and sodium laureth sulfate (and) cocamide DEA (and) cocamidopropyl betaine (and) glycol stearate.

Sodium sulfacetamide is a sulfonamide with antibacterial activity. Sodium sulfacetamide is C8H9N2NaO3S·H2O with molecular weight of 254.24. Chemically, sodium sulfacetamide is N-[(4-aminophenyl) sulfonyl]-acetamide, monosodium salt, monohydrate. The structural formula is:

Sodium sulfacetamide is an odorless, white, crystalline powder with a bitter taste. It is freely soluble in water, sparingly soluble in alcohol, while practically insoluble in benzene, in chloroform and in ether.

CLINICAL PHARMACOLOGY:

Sodium Sulfacetamide exerts a bacteriostatic effect against sulfonamide sensitive Gram-positive and Gram-negative microorganisms commonly isolated from secondary cutaneous pyogenic infections. It acts by restricting the synthesis of folic acid required by bacteria for growth, by its competition with para-aminobenzoic acid. There is no clinical data available on the degree and rate of systemic absorption of this product when applied to the skin or scalp. However, significant absorption of sodium sulfacetamide through the skin has been reported.

The following in vitro data is available but the clinical significance is unknown. Organisms that show susceptibility to sodium sulfacetamide are: Streptococci, Staphylococci, E. coli, Klebsiella pneumoniae, Pseudomonas pyocyanea, Salmonella species, Proteus vulgaris, Nocardia and Actinomyces.

INDICATIONS:

This product is intended for topical application in the following scaling dermatoses: seborrheic dermatitis and seborrhea sicca (dandruff). It also is indicated for the treatment of secondary bacterial infections of the skin due to organisms susceptible to sulfonamides.

CONTRAINDICATIONS:

This product is contraindicated in persons with known or suspected hypersensitivity to any of the ingredients of the product. This product is not to be used by patients with kidney disease.

WARNINGS:

Sulfonamides are known to cause Stevens-Johnson syndrome in hypersensitive individuals. Stevens-Johnson syndrome also has been reported following the use of sodium sulfacetamide topically. Cases of drug-induced systemic lupus erythematosus from topical sulfacetamide also have been reported. In one of these cases, there was a fatal outcome. KEEP OUT OF THE REACH OF CHILDREN.

PRECAUTIONS:

FOR EXTERNAL USE ONLY. NOT FOR OPHTHALMIC USE.

General: Nonsusceptible organisms, including fungi, may proliferate with the use of this preparation.

Although rare, sensitivity to sodium sulfacetamide may occur. Therefore, caution and careful supervision should be observed when prescribing this drug for patients who may be prone to hypersensitivity to topical sulfonamides. If the use of this product produces signs of hypersensitivity or other untoward reactions, discontinue use of the preparation. Patients should be carefully observed for possible local irritation or sensitization during long-term therapy. Systemic toxic reactions such as agranulocytosis, acute hemolytic anemia, purpura hemorrhagica, drug fever, jaundice and contact dermatitis indicate hypersensitivity to sulfonamides. Particular caution should be employed if areas of denuded or abraded skin are involved. Systemic absorption of topical sulfonamides is greater following application to large, infected, abraded, denuded or severely burned areas. Under these circumstances, any of the adverse effects produced by the systemic administration of these agents could potentially occur, and appropriate observations and laboratory determinations should be performed.

Information for Patients: Patients should discontinue the use of this product if the condition becomes worse or if a rash develops in the area being treated or elsewhere. The use of this product also should be discontinued promptly and the physician notified if any arthritis, fever or sores in the mouth develop. Avoid contact with eyes, lips and mucous membranes.

Drug Interactions: This product is incompatible with silver preparations.

Carcinogenesis, Mutagenesis and Impairment of Fertility: Long-term animal studies for carcinogenic potential have not been performed on this product to date. Studies on reproduction and fertility also have not been performed. Chromosomal nondisjunction has been reported in the yeast, Saccharomyces cerevisiae, following application of sodium sulfacetamide. The significance of this finding to the topical use of sodium sulfacetamide in the human is unknown.

Pregnancy: Category C. Animal reproduction studies have not been conducted with this product. It is also not known whether this product can affect reproduction capacity or cause fetal harm when administered to a pregnant woman. This product should be used by a pregnant woman only if clearly needed or when potential benefits outweigh potential hazards to the fetus.

Nursing Mothers: It is not known whether this drug is excreted in human milk. Because many drugs are excreted in human milk, caution should be exercised when this product is administered to a nursing woman.

Pediatric Use: Safety and effectiveness in children under the age of 12 years have not been established.

ADVERSE REACTIONS:

Reports of irritation and hypersensitivity to sodium sulfacetamide are uncommon. The following adverse reactions, reported after administration of sterile ophthalmic sodium sulfacetamide, are noteworthy: instances of Stevens-Johnson syndrome and instances of local hypersensitivity which progressed to a syndrome resembling systemic lupus erythematosus; in one case a fatal outcome was reported (see WARNINGS).

OVERDOSAGE:

The oral LD50 of sulfacetamide in mice is 16.5 g/kg. In the event of overdosage, emergency treatment should be started immediately.

Manifestations: Overdosage may cause nausea and vomiting. Large oral overdosage may cause hematuria, crystalluria and renal shutdown due to the precipitation of sulfa crystals in the renal tubules and the urinary tract. For treatment, contact your local Poison Control Center or your doctor.

DOSAGE AND ADMINISTRATION:

Seborrheic dermatitis including seborrhea sicca - Shake well before using. Wash affected areas twice daily (morning and evening) or as directed by your physician. Avoid contact with eyes or mucous membranes. Wet skin and liberally apply to areas to be cleansed, massage gently into skin working into a full lather, rinse thoroughly, pat dry and repeat after 10 to 20 seconds. Rinsing with plain water will remove any excess medication. Repeat application as described above for 8 to 10 days or as directed by your physician. If skin dryness occurs it may be controlled by rinsing cleanser off sooner or using less frequently. Regular shampooing following the use of this product is not necessary, but the hair should be shampooed at least once a week. As the condition subsides, the interval between applications may be lengthened. Applications once or twice weekly or every other week may prevent recurrence. Should the condition recur after stopping therapy, the application of this product should be reinitiated as at the beginning of treatment.

Secondary cutaneous bacterial infections - Shake well before using. Wash affected areas twice daily (morning and evening) or as directed by your physician. Avoid contact with eyes or mucous membranes. Wet skin and liberally apply to areas to be cleansed, massage gently into skin for 10 to 20 seconds working into a full lather, rinse thoroughly and pat dry. Rinsing with plain water will remove any excess medication. Repeat application as described above for 8 to 10 days or as directed by your physician. If skin dryness occurs it may be controlled by rinsing cleanser off sooner or using less frequently.

STORAGE:

Store at 20°C to 25°C (68°F to 77°F), excursions permitted between 15°C and 30°C (between 59°F and 86°F). Brief exposure to temperatures up to 40°C (104°F) may be tolerated provided the mean kinetic temperature does not exceed 25°C (77°F); however, such exposure should be minimized.

NOTICE: Protect from freezing and excessive heat. The product may tend to darken slightly on storage. Slight discoloration does not impair the efficacy or safety of the product. Keep bottle tightly closed.

Occasionally, a slight discoloration of fabric may occur when an excessive amount of the product is used and comes in contact with white fabrics. This discoloration, however, presents no problem, as it is readily removed by ordinary laundering without bleaches.

HOW SUPPLIED:

This product is supplied in the following size(s):
6 fl. oz. (177 mL) bottles, NDC 44523-613-06

12 fl. oz. (355 mL) bottles, NDC 44523-606-12

16 fl. oz. (480 mL) bottles, NDC 44523-606-16

To report a serious adverse event or obtain product information, call 1-866-762-2365.

Manufactured for:
BIOCOMP PHARMA, INC.
San Antonio, TX 78230 1355

L70612R0425